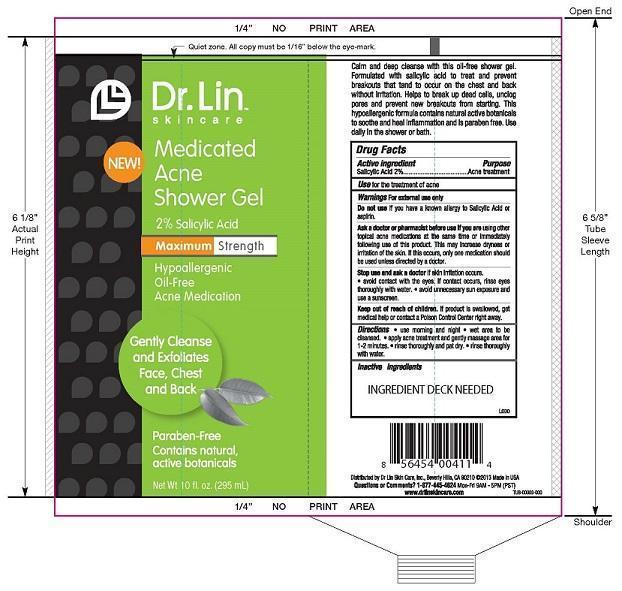 DRUG LABEL: MEDICATED ACNE SHOWER
NDC: 58876-108 | Form: GEL
Manufacturer: DR LIN SKINCARE
Category: otc | Type: HUMAN OTC DRUG LABEL
Date: 20140711

ACTIVE INGREDIENTS: SALICYLIC ACID 2 g/100 mL
INACTIVE INGREDIENTS: WATER; SODIUM C14-16 OLEFIN SULFONATE; SODIUM LAURETH SULFATE; COCAMIDOPROPYL BETAINE; SODIUM LAURYL SULFOACETATE; PEG-150 DISTEARATE; PHENOXYETHANOL; METHYLISOTHIAZOLINONE; AMINOMETHYLPROPANOL; SODIUM CHLORIDE; GLYCERIN; ALLANTOIN

ACTIVE INGREDIENT

SALICYLIC ACID 2%

PURPOSE

ACNE TREATMENT

USE

FOR THE TREATMENT OF ACNE

WARNINGS

FOR EXTERNAL USE ONLY

DO NOT USE IF YOU HAVE KNOWN ALLERGY TO SALICYLIC ACID OR ASPERIN.

ASK A DOCTOR OR PHARMACIST BEFORE USE IF YOU ARE USING OTHER TOPICAL ACNE MEDICATIONS AT THE SAME TIME OR IMMEDIATELY FOLLOWING USE OF THIS PRODUCT. THIS MAY INCREASE DRYNESS OR IRRITATION OF TH SKIN. IF THIS OCCURS, ONLY ONE MEDICATION SHOULD BE USED UNLESS DIRECTED BY A DOCTOR.

STOP USE ND ASK A DOCTOR IF SKIN IRRITATION OCCURS.

- AVOID CONTACT WITH THE EYES. IF CONTACT OCCURS, RINSE EYES THOROUGHLY WITH WATER.
- AVOID UNNECESSARY SUN EXPOSURE AND USE A SUNSCREEN.

KEEP OUT OF REACH OF CHILDREN. IF PRODUCT IS SWALLOWED, GET MEDICL HELP OR CONTACT A POISON CONTROL CENTER RIGHT AWAY.

DIRECTIONS

- USE MORNING AND NIGHT.
- WET AREA TO BE CLEANSED.
- APPLY ACNE TREATMENT ND GENTLY MASSAGE AREA FOR 1-2 MINUTES..
- RINSE THOROUGHLY AND PAT DRY.
- RINSE THOROUGHLY WITH WATER..

INACTIVE INGREDIENTS

WATER, SODIUM C14-16 OLEFIN SULFONATE, SODIUM LAURETH SULFATE, COCAMIDOPROPYL BETAINE, SODIUM LAURYL SULFOACETATE, PEG-150 DISTEARATE, PHENOXYETHANOL, METHYLISOTHIAZOLINONE, AMINOMETHYL PROPANOL, SODIUM CHLORIDE, GLYCERIN, ALLANTOIN

QUESTIONS OR COMMENTS? 1-877-445-4624